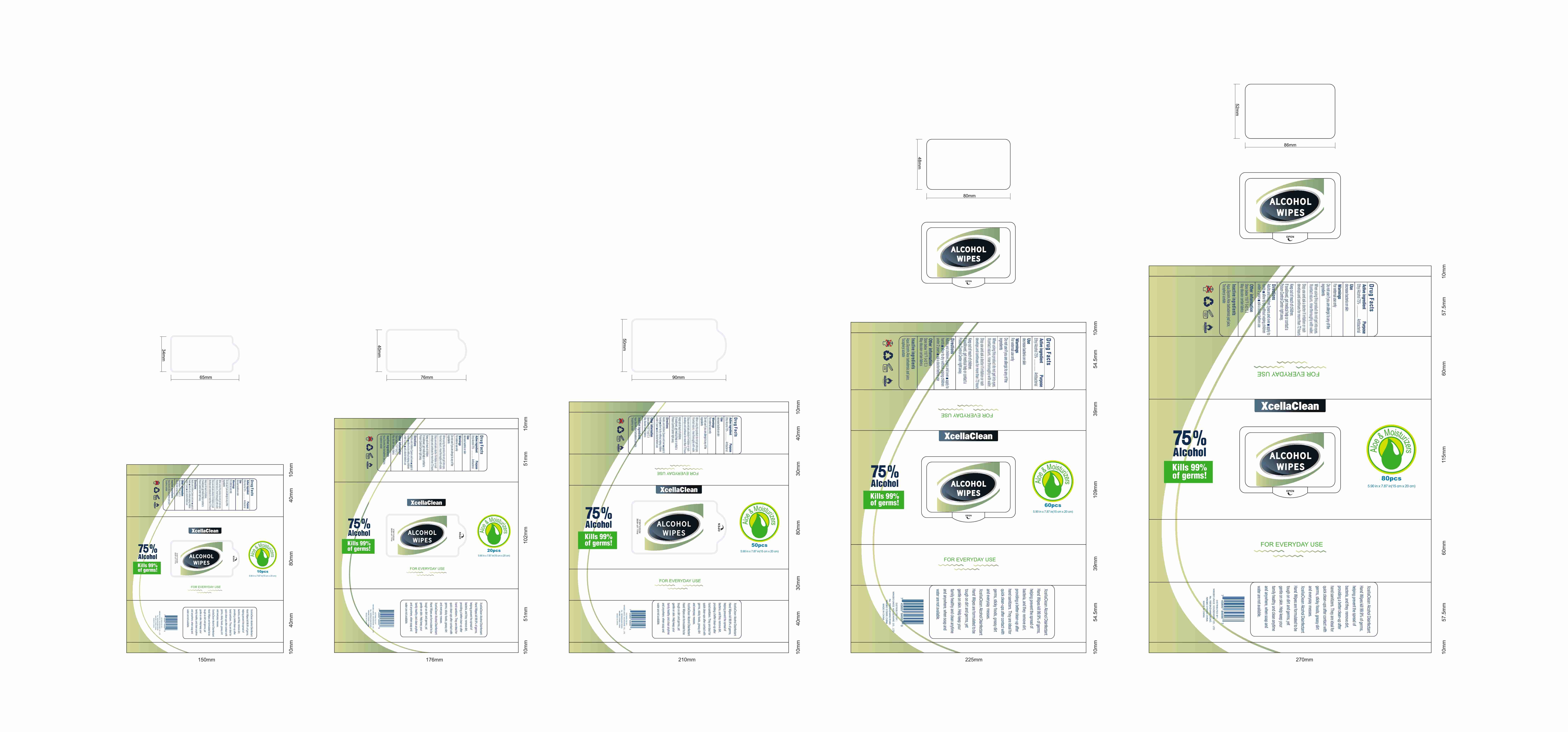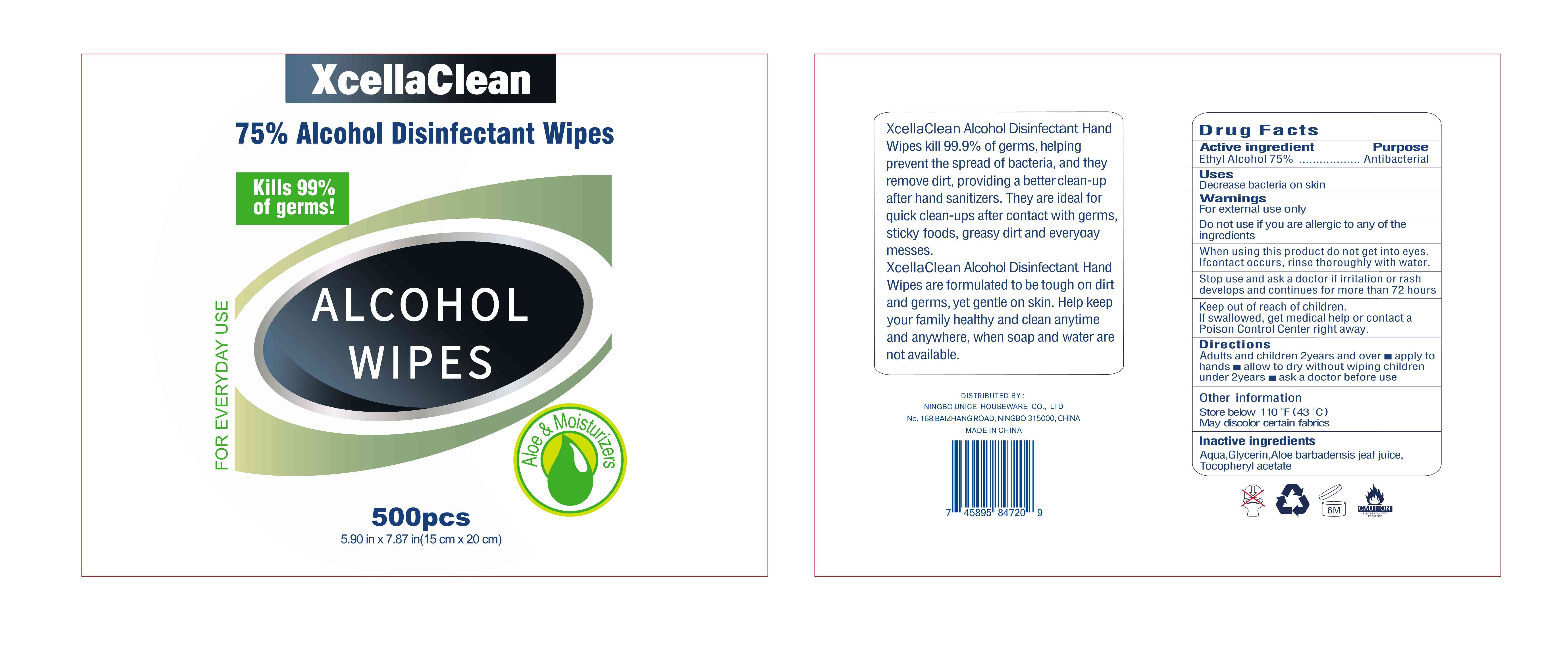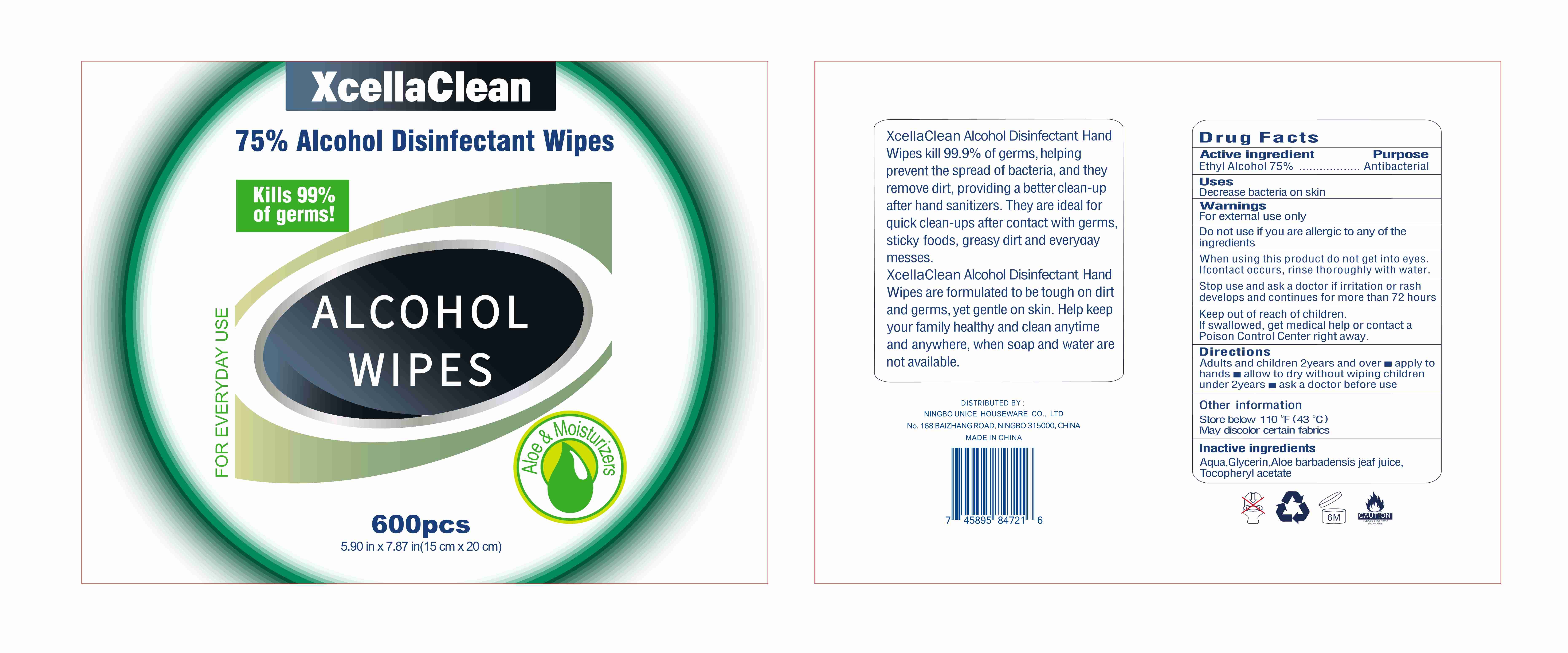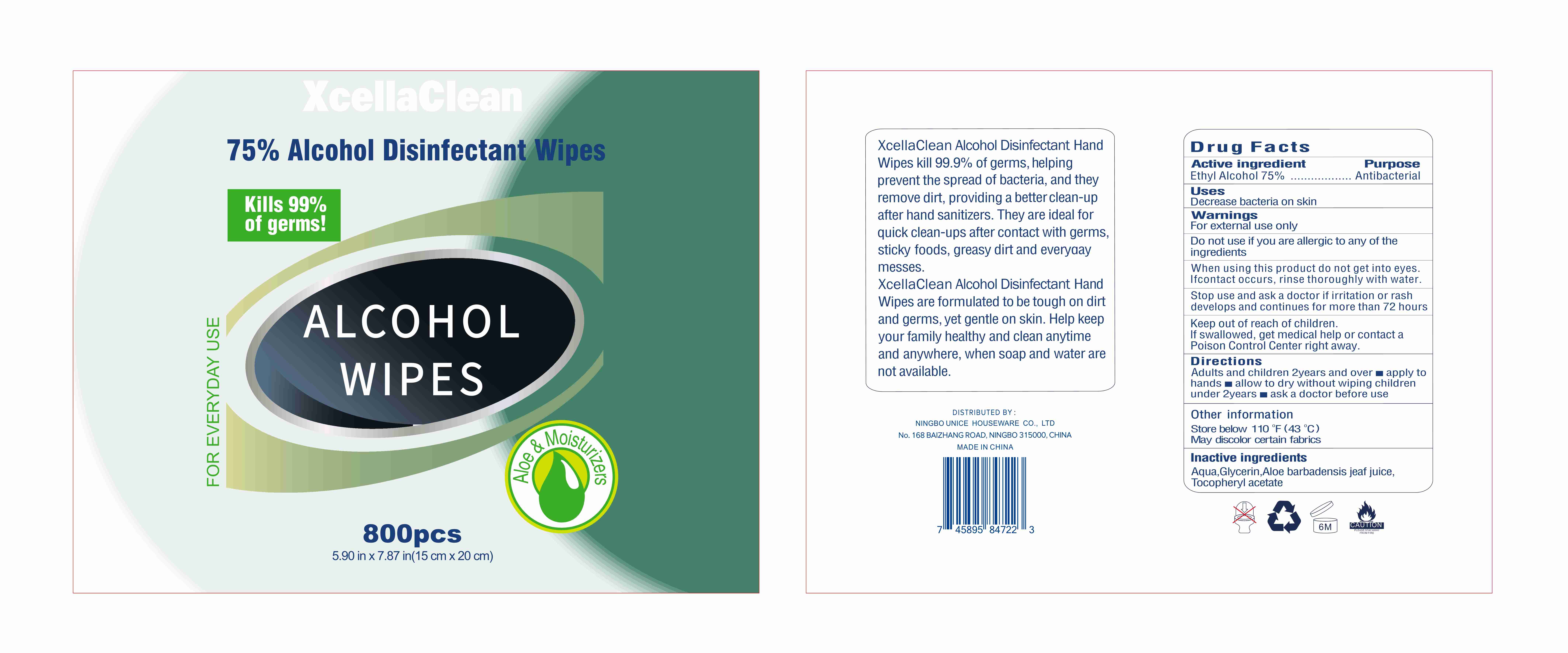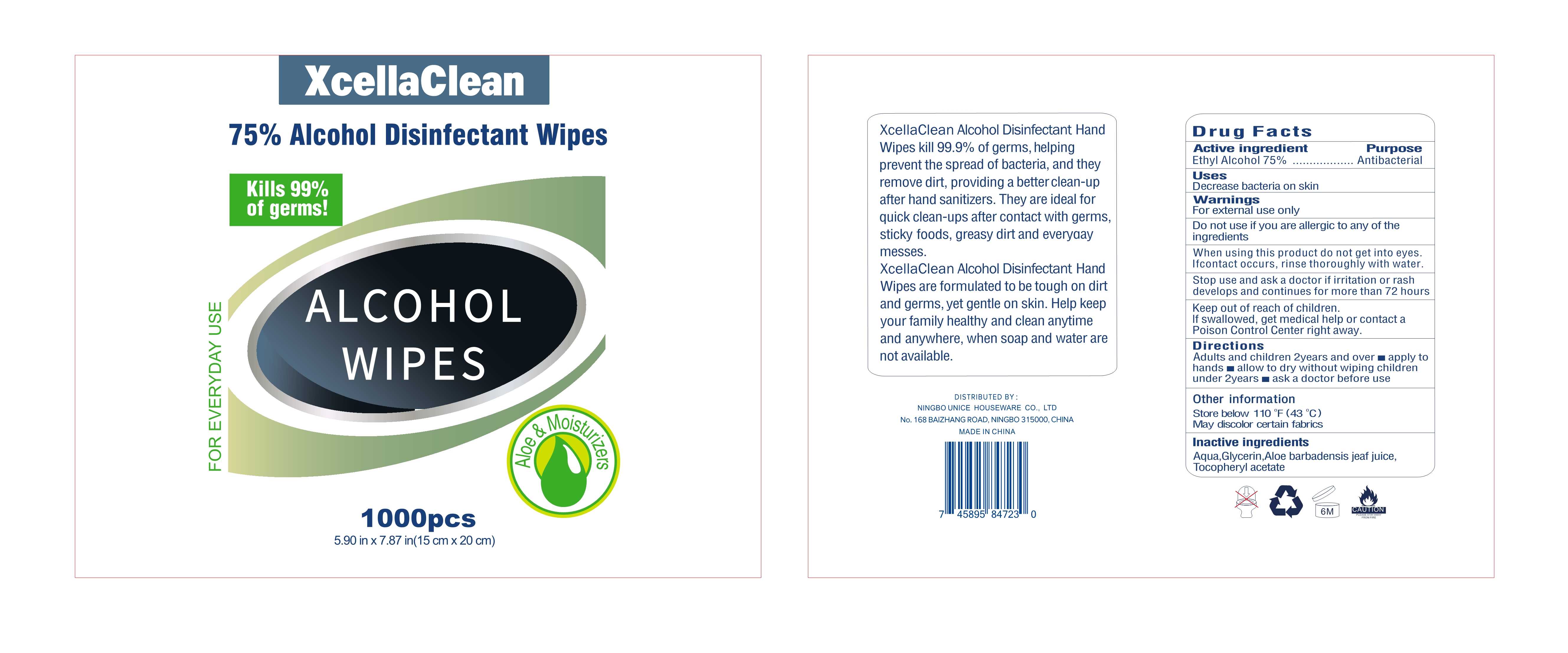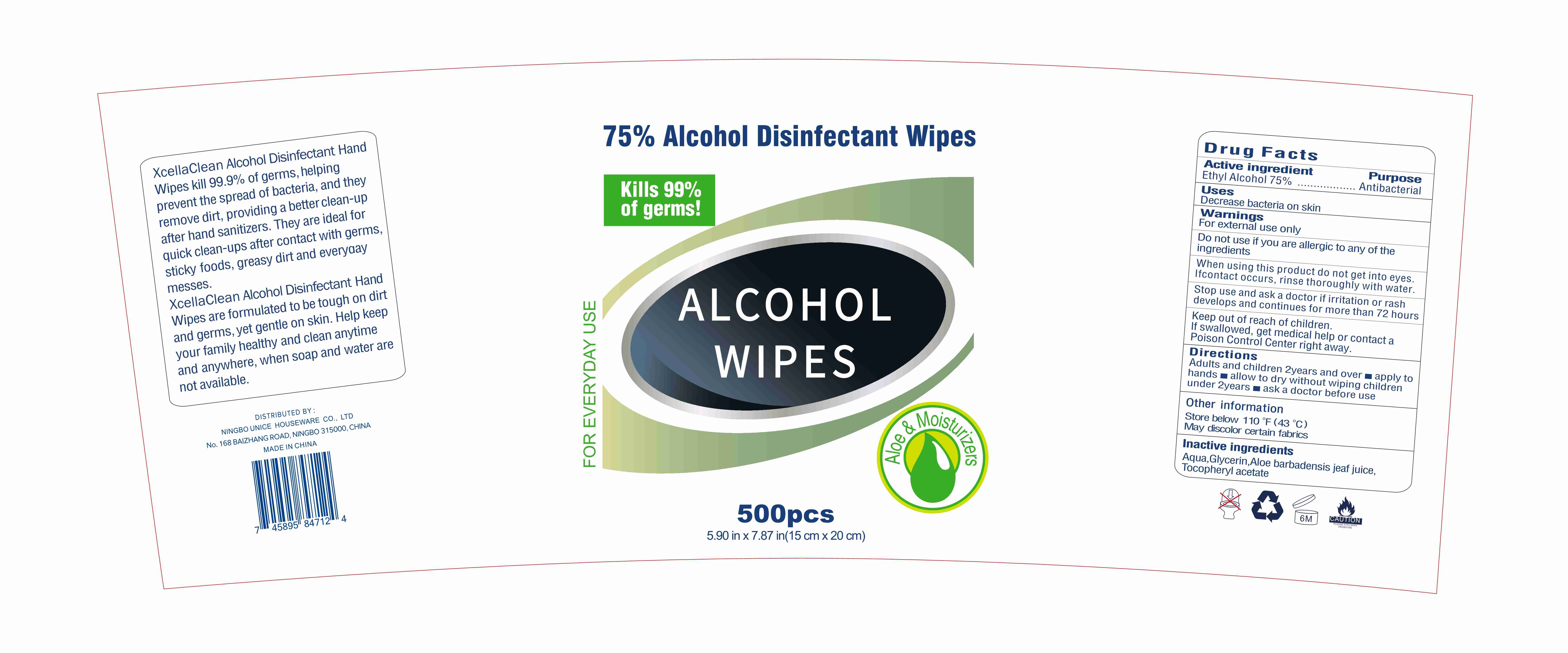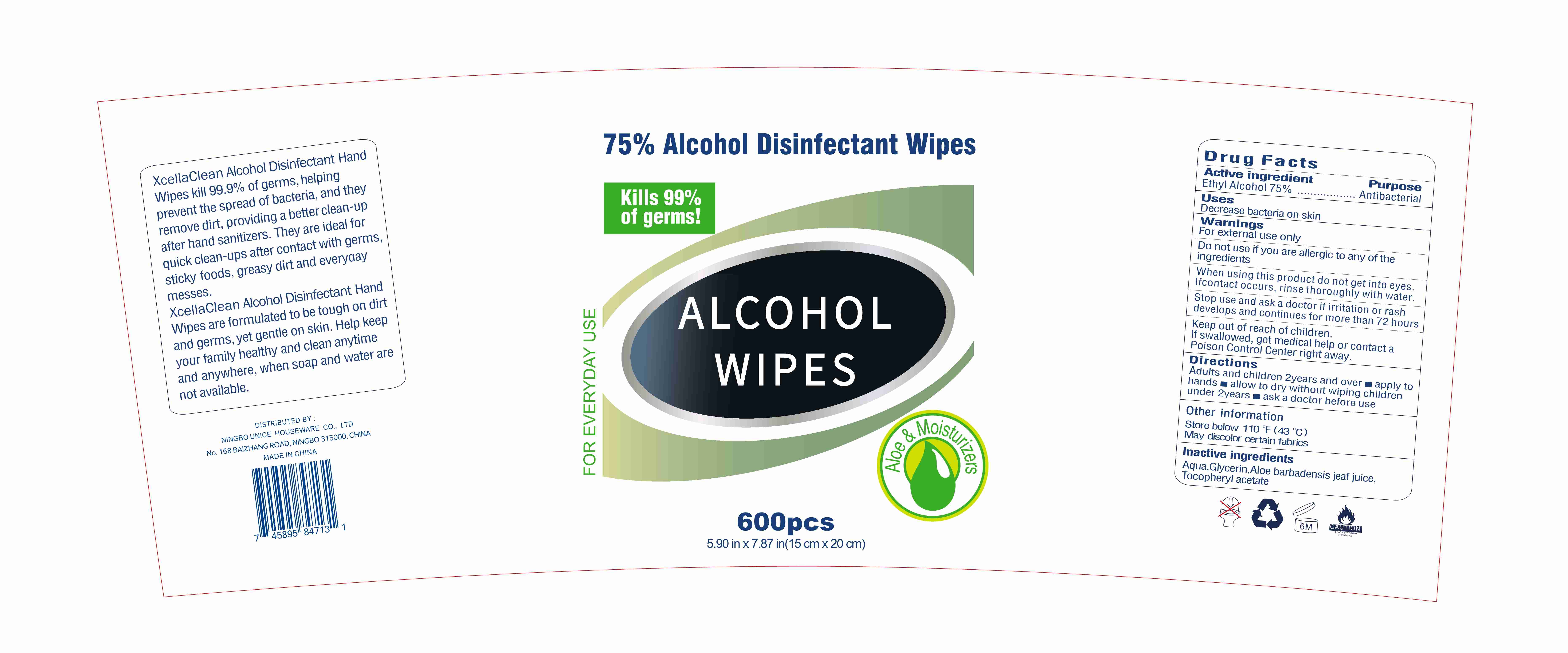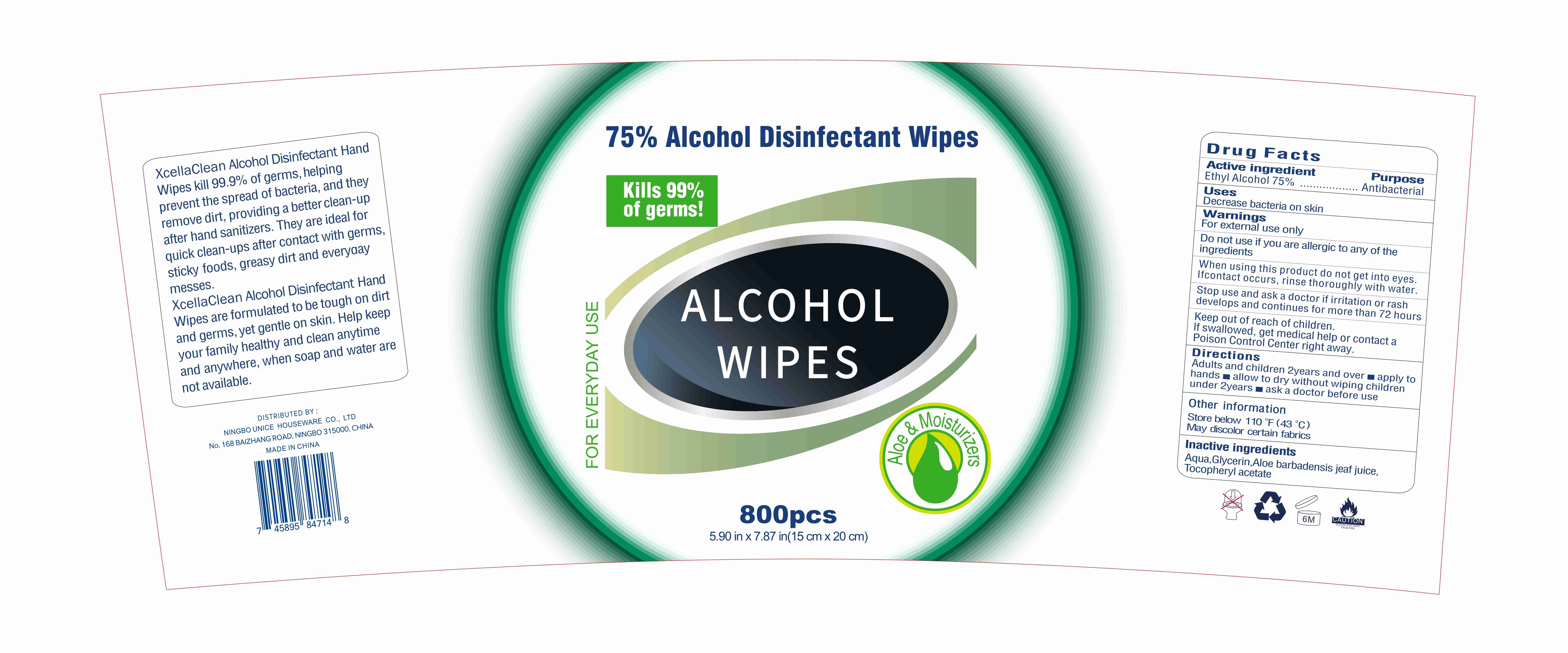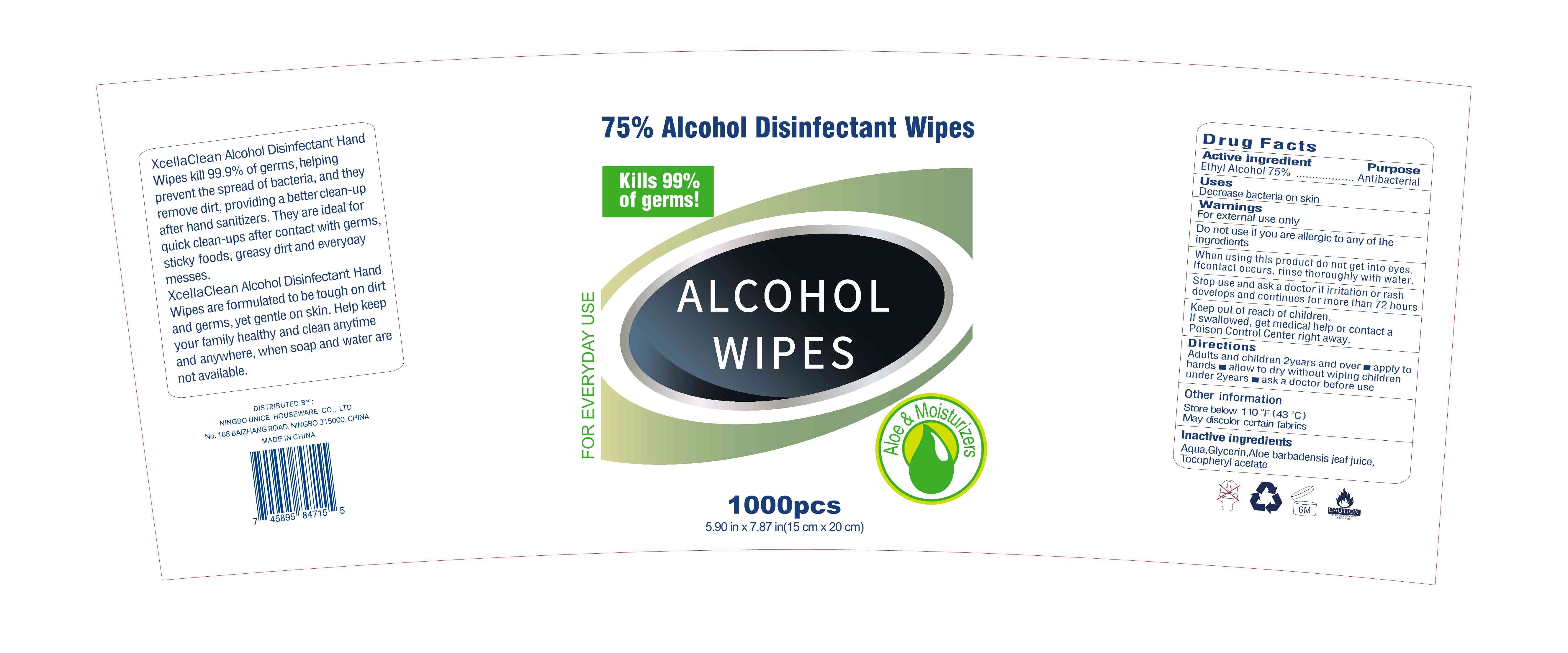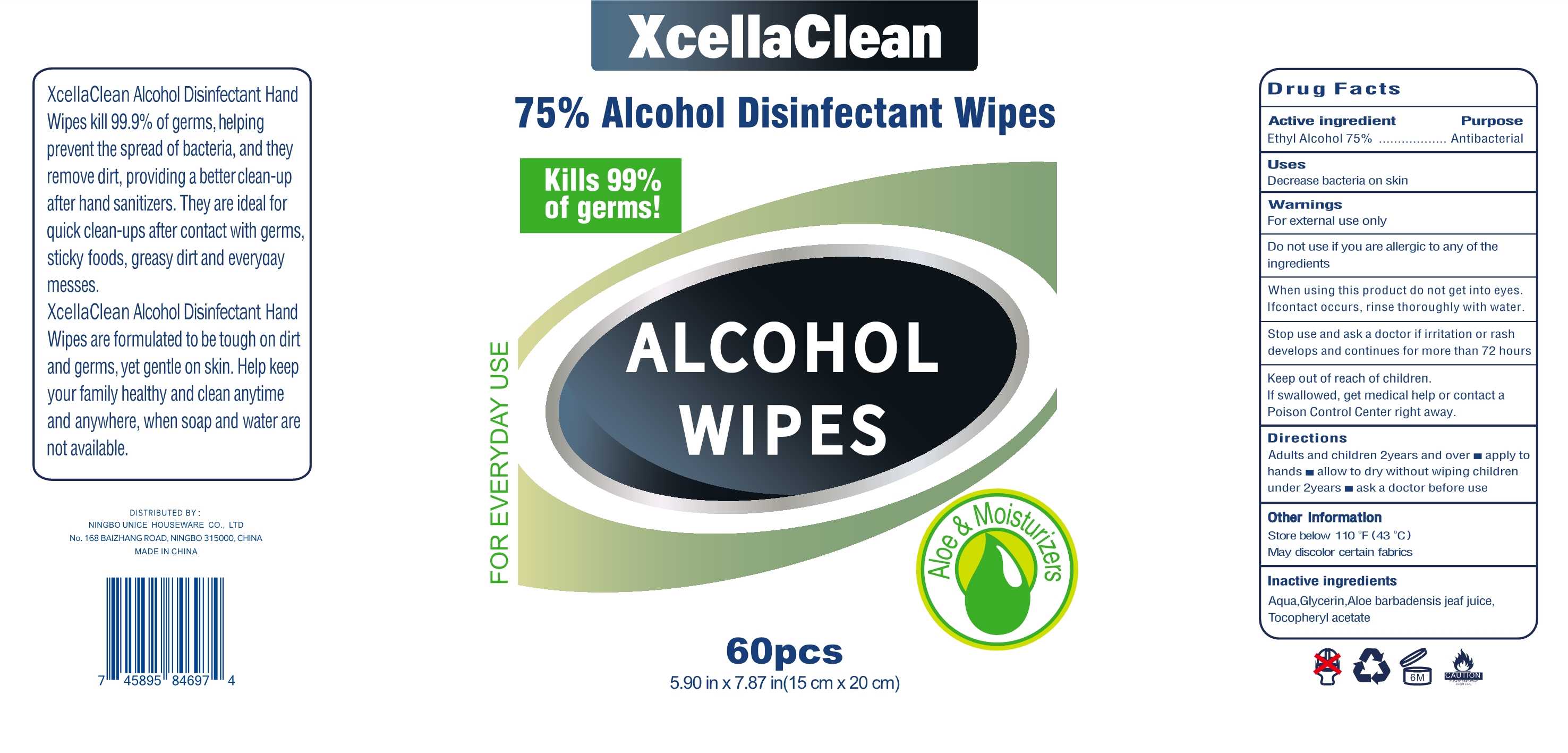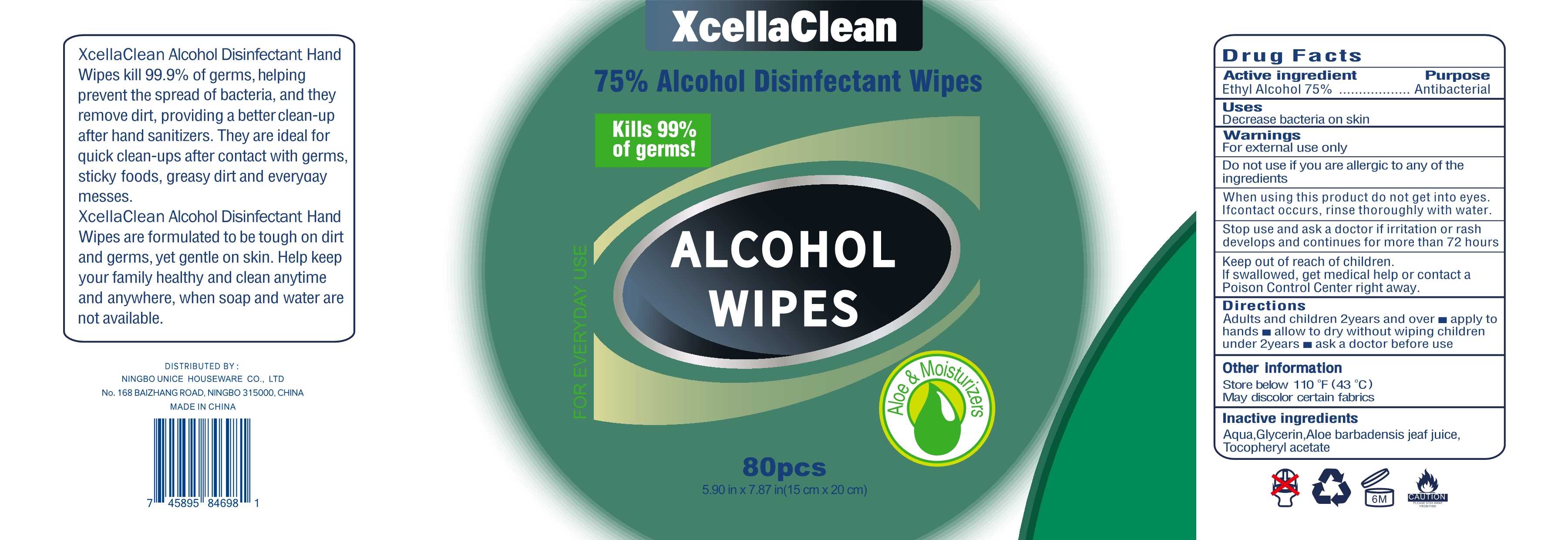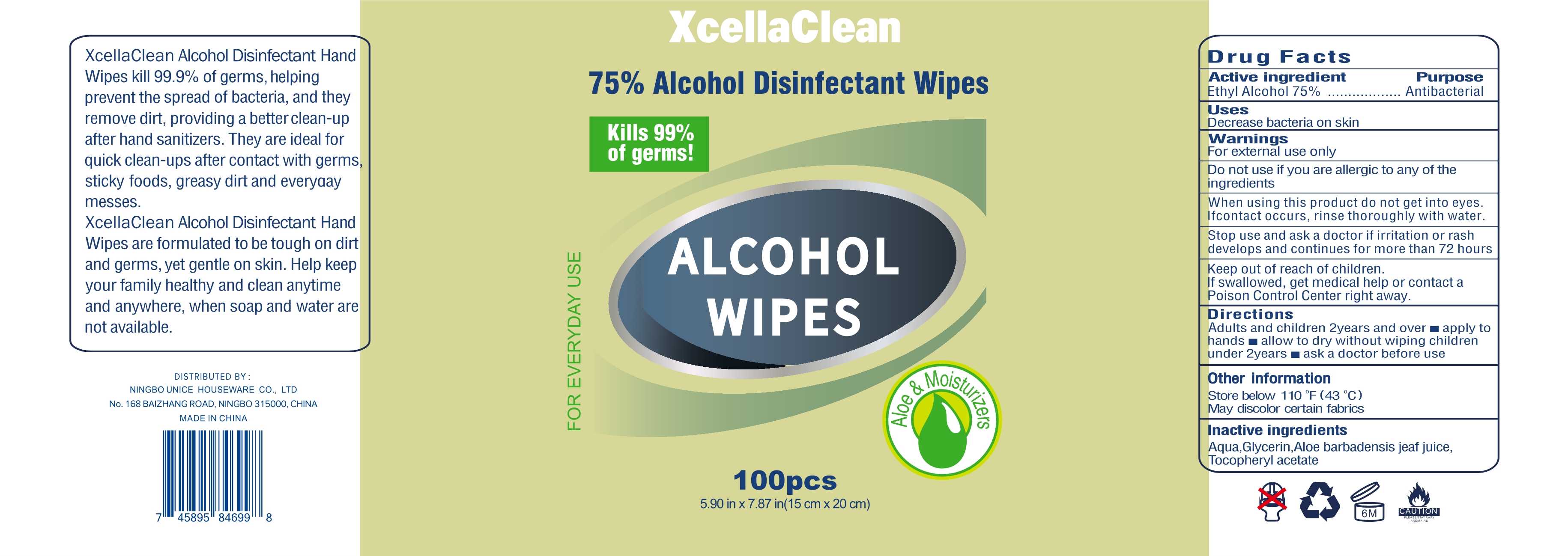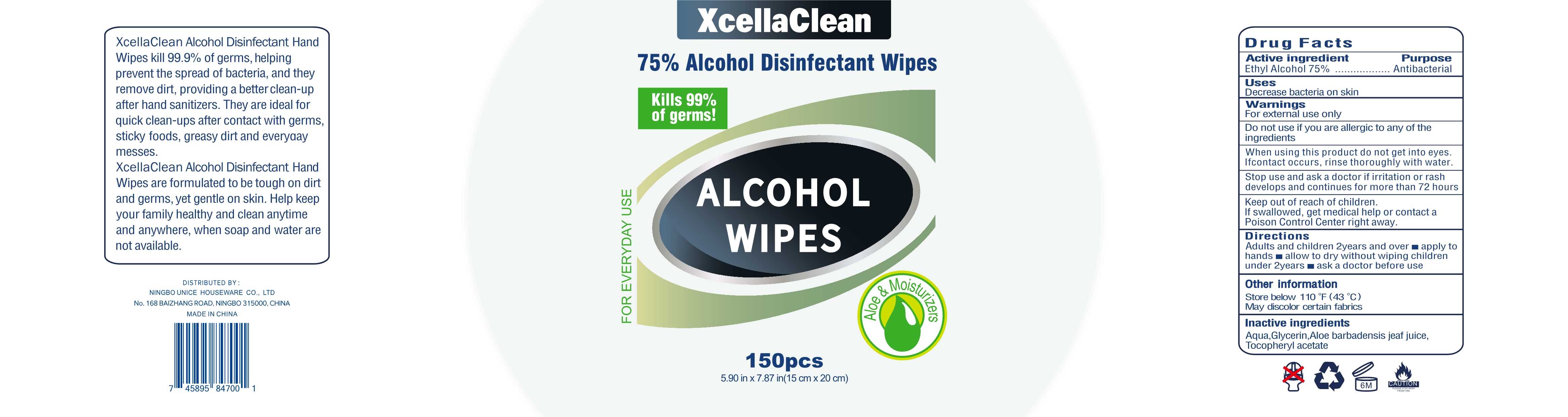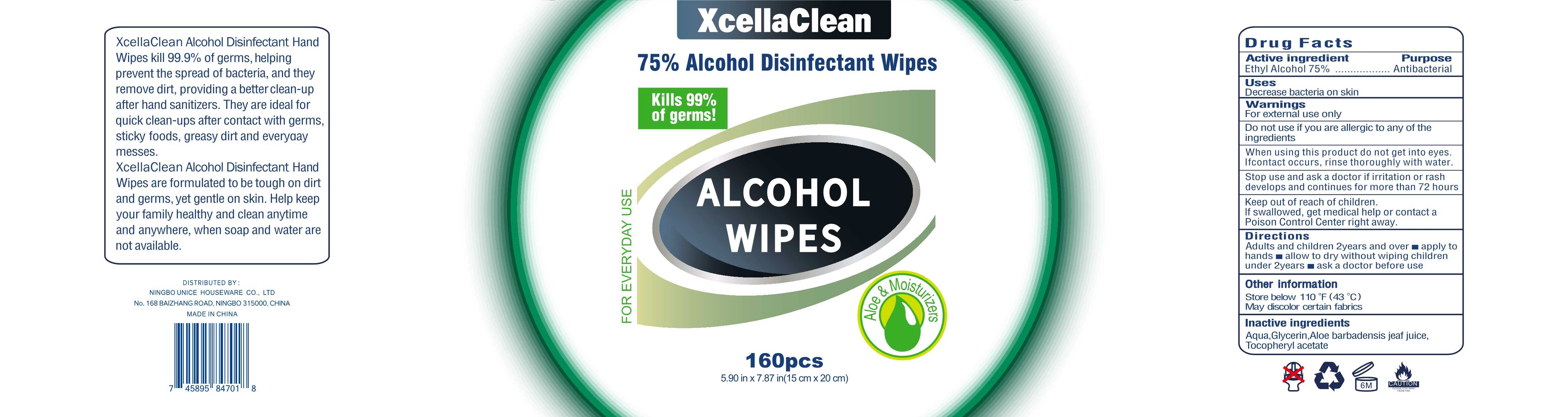 DRUG LABEL: 75%Alcohol Disinfectant Wipes
NDC: 77765-012 | Form: CLOTH
Manufacturer: Hangzhou Beitai Daily Commodity Co., Ltd.
Category: otc | Type: HUMAN OTC DRUG LABEL
Date: 20200830

ACTIVE INGREDIENTS: ALCOHOL 75 1/100 1
INACTIVE INGREDIENTS: .ALPHA.-TOCOPHEROL ACETATE; GLYCERIN; ALOE VERA LEAF; WATER

77765-012
75%Alcohol Disinfectant Wipes

Active Ingredient(s)

Ethyl Alcohol 75%

Purpose

Antiseptic

Use

Decrease bacteria on skin

Warnings

For external use only

Do not use if you are allergic to any of the ingredients

When using this product do not get into eyes.
Ifcontact occurs, rinse thoroughly with water.

Stop use and ask a doctor if irritation or rash develops and C1ont inues for more than 72 hours

Keep out of reach of children.
If swallowed, get medical help or contact a
Poison Control Center right away.

Do not use if you are allergic to any of the ingredients

When using this product do not get into eyes.
If contact occurs, rinse thoroughly with water.

Stop use and ask a doctor if irritation or rash develops and C1ont inues for more than 72 hours

Keep out of reach of children.
If swallowed, get medical help or contact a
Poison Control Center right away.

Stop use and ask a doctor if irritation or rash develops and C1ont inues for more than 72 hours

Keep out of reach of children.
If swallowed, get medical help or contact a
Poison Control Center right away.

Directions

Adults and children 2years and over
apply to hands
allow to dry without wiping children under 2years
ask a doctor before use

Other information

Store below 110°F (43°C)
May discolor certain fabrics

Inactive ingredients

Aqua, Glycerin, Aloe barbadensis jeaf juice, Tocopheryl acetate